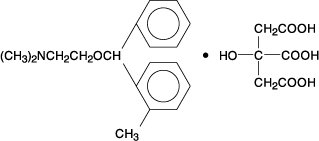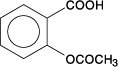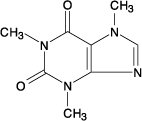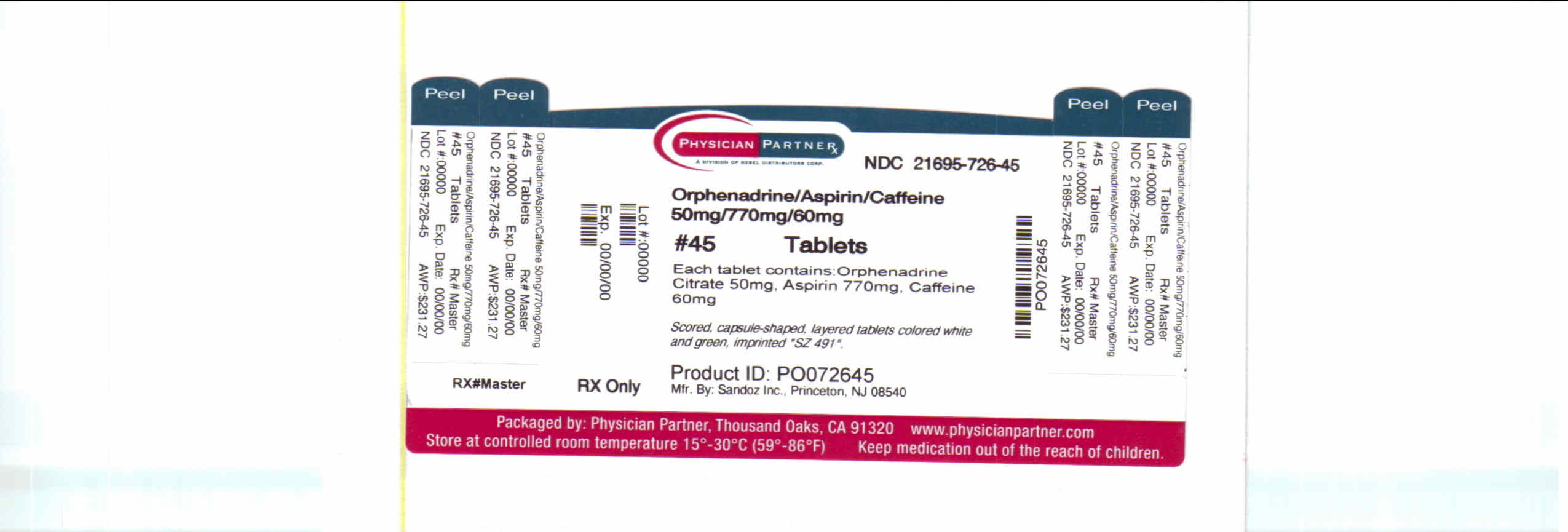 DRUG LABEL: Orphenadrine Citrate, Aspirin and Caffeine
NDC: 21695-726 | Form: TABLET, MULTILAYER
Manufacturer: Rebel Distributors Corp
Category: prescription | Type: HUMAN PRESCRIPTION DRUG LABEL
Date: 20101022

ACTIVE INGREDIENTS: ORPHENADRINE CITRATE 50 mg/1 1; ASPIRIN 770 mg/1 1; CAFFEINE 60 mg/1 1
INACTIVE INGREDIENTS: ANHYDROUS LACTOSE; CROSCARMELLOSE SODIUM; FD&C BLUE NO. 1; D&C YELLOW NO. 10; CELLULOSE, MICROCRYSTALLINE; POVIDONE; SILICON DIOXIDE; SODIUM LAURYL SULFATE; STARCH, CORN; STEARIC ACID

Orphenadrine Citrate, Aspirin and Caffeine Tablets

DESCRIPTION

Each tablet, for oral administration, contains Orphenadrine Citrate USP, 25 mg or 50 mg, Aspirin USP, 385 mg or 770 mg, Caffeine USP, 30 mg or 60 mg.

Orphenadrine citrate, N, N-Dimethyl-2-[(o-methyl-α-phenylbenzyl)oxy]ethylamine citrate (1:1), is a centrally acting (brain stem) compound. It occurs as a white, practically odorless, crystalline powder, having a bitter taste. Its molecular formula is C18H23NO.C6H8O7 with a molecular weight of 461.51. The structural formula is shown below.

Aspirin, salicylic acid acetate, is a non-opiate analgesic, anti-inflammatory and antipyretic agent. It occurs as a white, crystalline tabular or needle like powder and is odorless or has a faint odor. Its molecular formula is C9H8O4, with a molecular weight of 180.16. The structural formula is shown below.

Caffeine, 1,3,7-trimethylxanthine, is a central nervous system stimulant which occurs as a white powder or white glistening needles. It also has a bitter taste. Its molecular formula is C8H10N4O2, with a molecular weight of 194.19. The structural formula is shown below.

Each tablet contains the following inactive ingredients: colloidal silicon dioxide, corn starch, croscarmellose sodium, FD&C Blue No. 1, FD&C Yellow No. 10, anhydrous lactose, microcrystalline cellulose, povidone, pregelatinized starch, stearic acid, and sodium lauryl sulfate.

CLINICAL PHARMACOLOGY

Orphenadrine citrate is a centrally acting (brain stem) compound which in animals selectively blocks facilitatory functions of the reticular formulation. Orphenadrine does not produce myoneural block, nor does it affect crossed extensor reflexes. Orphenadrine prevents nicotine-induced convulsions but not those produced by strychnine.

Chronic administration of Orphenadrine Citrate, Aspirin, and Caffeine to dogs and rats has revealed no drug-related toxicity. No blood or urine changes were observed, nor were there any macroscopic or microscopic pathological changes detected. Extensive experience with combinations containing aspirin and caffeine has established them as safe agents. The addition of orphenadrine citrate does not alter the toxicity of aspirin and caffeine.

The mode of therapeutic action of orphenadrine has not been clearly identified, but may be related to its analgesic properties. Orphenadrine citrate also possesses anticholinergic actions.

INDICATIONS AND USAGE

1. Symptomatic relief of mild to moderate pain of acute musculoskeletal disorders.
2. The orphenadrine component is indicated as an adjunct to rest, physical therapy, and other measures for the relief of discomfort associated with acute painful musculoskeletal conditions.
  The mode of action of orphenadrine has not been clearly identified, but may be related to its analgesic properties. Orphenadrine Citrate, Aspirin, and Caffeine Tablets do not directly relax tense skeletal muscles in man.

CONTRAINDICATIONS

Because of the mild anti-cholinergic effect of orphenadrine, Orphenadrine Citrate, Aspirin, and Caffeine Tablets should not be used in patients with glaucoma, pyloric or duodenal obstruction, achalasia, prostatic hypertrophy, or obstructions at the bladder neck. Orphenadrine Citrate, Aspirin, and Caffeine Tablets are also contraindicated in patients with myasthenia gravis and in patients known to be sensitive to aspirin or caffeine.

The drug is contraindicated in patients who have demonstrated a previous hypersensitivity to the drug.

WARNINGS

Reye’s Syndrome may develop in individuals who have chicken pox, influenza, or flu symptoms. Some studies suggest possible association between the development of Reye’s Syndrome and the use of medicines containing salicylate or aspirin. Orphenadrine Citrate, Aspirin, and Caffeine Tablets contain aspirin and therefore are not recommended for use in patients with chicken pox, influenza, or flu symptoms. Orphenadrine Citrate, Aspirin, and Caffeine Tablets may impair the ability of the patient to engage in potentially hazardous activities such as operating machinery or driving a motor vehicle: ambulatory patients should therefore be cautioned accordingly.

Aspirin should be used with extreme caution in the presence of peptic ulcers and coagulation abnormalities.

Usage in Pregnancy

Since safety of the use of this preparation in pregnancy, during lactation, or in the child-bearing age has not been established, use of the drug in such patients requires that the potential benefits of the drug be weighed against its possible hazard to the mother and child.

Usage in Children

The safe and effective use of this drug in children has not been established. Usage of this drug in children under 12 years of age is not recommended.

PRECAUTIONS

Confusion, anxiety and tremors have been reported in a few patients receiving propoxyphene and orphenadrine concomitantly. As these symptoms may be simply due to an additive effect, reduction of dosage and/or discontinuation of one or both agents is recommended in such cases.

Safety of continuous long term therapy with Orphenadrine Citrate, Aspirin, and Caffeine Tablets has not been established; therefore, if Orphenadrine Citrate, Aspirin, and Caffeine Tablets are prescribed for prolonged use, periodic monitoring of blood, urine and liver function values is recommended.

ADVERSE REACTIONS

Side effects of Orphenadrine Citrate, Aspirin, and Caffeine Tablets are those seen with aspirin and caffeine or those usually associated with mild anticholinergic agents. These may include tachycardia, palpitation, urinary hesitancy or retention, dry mouth, blurred vision, dilation of the pupil, increased intraocular tension, weakness, nausea, vomiting, headache, dizziness, constipation, drowsiness, and rarely, urticaria and other dermatoses. Infrequently, an elderly patient may experience some degree of confusion. Mild central excitation and occasional hallucinations may be observed. These mild side effects can usually be eliminated by reduction in dosage. One case of aplastic anemia associated with the use of Orphenadrine Citrate, Aspirin, and Caffeine Tablets has been reported. No causal relationship has been established. Rare G.I. hemorrhage due to aspirin content may be associated with the administration of Orphenadrine Citrate, Aspirin, and Caffeine Tablets. Some patients may experience transient episodes of lightheadedness, dizziness or syncope.

DOSAGE AND ADMINISTRATION

Orphenadrine Citrate, Aspirin, and Caffeine Tablets, 25 mg/385 mg/30 mg: Adults 1 to 2 tablets 3 to 4 times daily.

Orphenadrine Citrate, Aspirin, and Caffeine Tablets, 50 mg/770 mg/60 mg: Adults 1/2 to 1 tablet 3 to 4 times daily.

HOW SUPPLIED

Orphenadrine Citrate, Aspirin, and Caffeine Tablets, 50 mg/770 mg/60 mg are scored, capsule-shaped, layered tablets colored white and green, imprinted SZ 491 and are supplied as:

NDC 21695-726-30 bottles of 30

NDC 21695-726-45 bottles of 45

Storage

Store at 20°-25°C (68°-77° F) (see USP Controlled Room Temperature).

Protect from moisture.

Sandoz Inc.

Princeton, NJ 08540

Repackaged by:

Rebel Distributors Corp

Thousand Oaks, CA 91320

50 mg/770 mg/60 mg Label

Orphenadrine

Citrate, Aspirin,

and Caffeine

Tablets

50 mg/770 mg/60 mg

Rx only